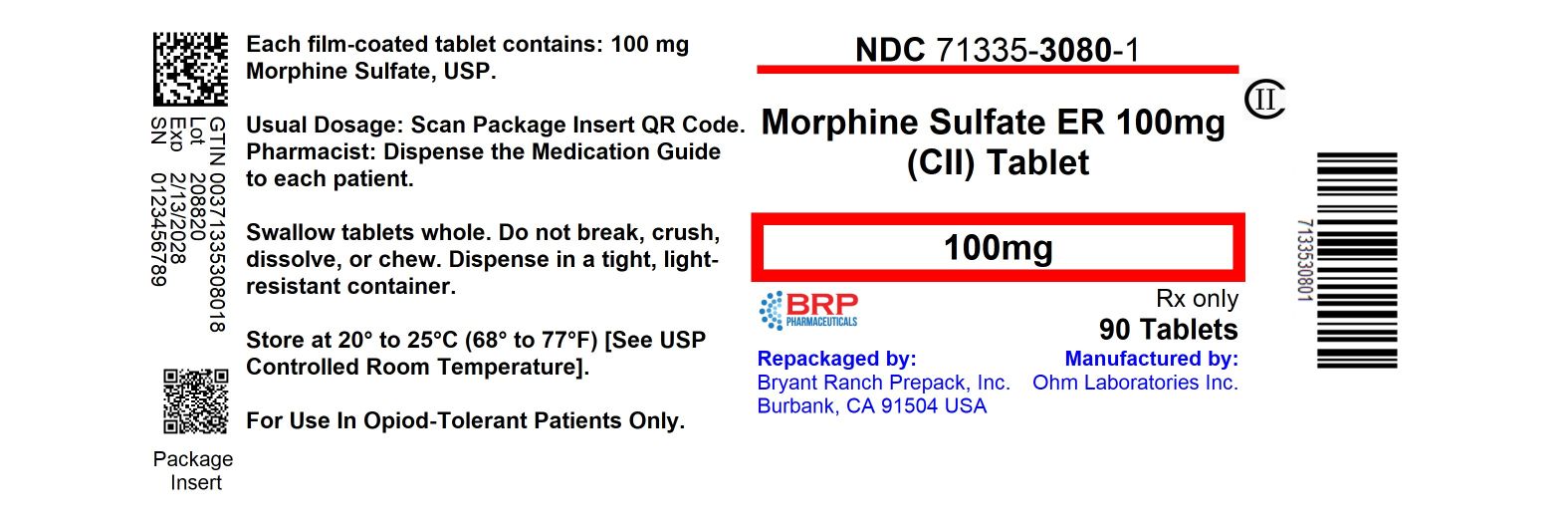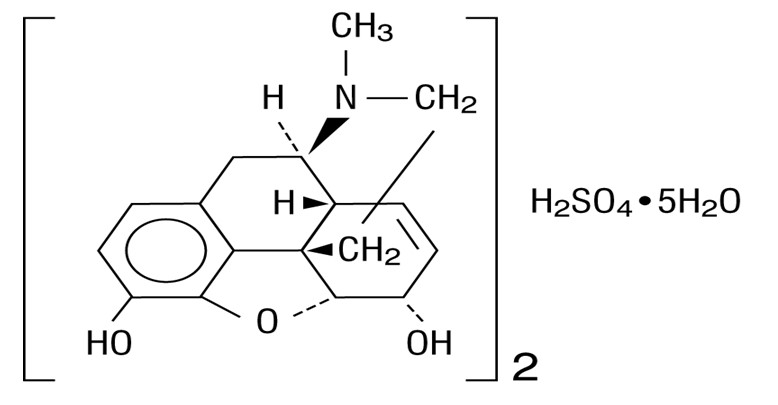 DRUG LABEL: Morphine sulfate
NDC: 71335-3080 | Form: TABLET, FILM COATED, EXTENDED RELEASE
Manufacturer: Bryant Ranch Prepack
Category: prescription | Type: HUMAN PRESCRIPTION DRUG LABEL
Date: 20260213
DEA Schedule: CII

ACTIVE INGREDIENTS: MORPHINE SULFATE 100 mg/1 1
INACTIVE INGREDIENTS: SILICON DIOXIDE; HYPROMELLOSE, UNSPECIFIED; LACTOSE MONOHYDRATE; MAGNESIUM STEARATE; POVIDONE, UNSPECIFIED; STEARIC ACID; TALC; TITANIUM DIOXIDE; FD&C BLUE NO. 2; FERROSOFERRIC OXIDE; FERRIC OXIDE YELLOW; POLYETHYLENE GLYCOL 400; POLYETHYLENE GLYCOL 4000

HIGHLIGHTS OF PRESCRIBING INFORMATION

These highlights do not include all the information needed to use MORPHINE SULFATE EXTENDED-RELEASE TABLETS safely and effectively. See full prescribing information for MORPHINE SULFATE EXTENDED-RELEASE TABLETS.
MORPHINE sulfate extended-release tablets, for oral use CII
Initial U.S. Approval: 1941

WARNING: ADDICTION, ABUSE, AND MISUSE; RISK EVALUATION AND MITIGATION STRATEGY (REMS); LIFE-THREATENING RESPIRATORY DEPRESSION; ACCIDENTAL INGESTION; NEONATAL OPIOID WITHDRAWAL SYNDROME; and RISKS FROM CONCOMITANT USE WITH BENZODIAZEPINES OR OTHER CNS DEPRESSANTS

See full prescribing information for complete boxed warning.

- Morphine sulfate exposes users to risks of addiction, abuse, and misuse, which can lead to overdose and death. Assess patient’s risk before prescribing, and monitor regularly for these behaviors and conditions. (5.1)
- To ensure that the benefits of opioid analgesics outweigh the risks of addiction, abuse, and misuse, the Food and Drug Administration (FDA) has required a Risk Evaluation and Mitigation Strategy (REMS) for these products. (5.2)
- Serious, life-threatening, or fatal respiratory depression may occur, especially during initiation or following a dose increase. To reduce the risk of respiratory depression, proper dosing and titration of morphine sulfate extended-release tablets are essential. Instruct patients to swallow morphine sulfate extended-release tablets whole to avoid exposure to a potentially fatal dose of morphine. (5.3)
- Accidental ingestion of morphine sulfate extended-release tablets, especially by children, can result in a fatal overdose of morphine. (5.3)
- Prolonged use of morphine sulfate during pregnancy can result in neonatal opioid withdrawal syndrome, which may be life-threatening if not recognized and treated. If prolonged opioid use is required in a pregnant woman, advise the patient of the risk of neonatal opioid withdrawal syndrome and ensure that appropriate treatment will be available. (5.4)
- Concomitant use of opioids with benzodiazepines or other central nervous system (CNS) depressants, including alcohol, may result in profound sedation, respiratory depression, coma, and death. Reserve concomitant prescribing for use in patients for whom alternative treatment options are inadequate; limit dosages and durations to the minimum required; and follow patients for signs and symptoms of respiratory depression and sedation. (5.5, 7)

RECENT MAJOR CHANGES

Boxed Warning 09/2023

Dosage and Administration (2.4, 2.6) 09/2023

Warnings and Precautions (5.1, 5.5) 09/2023

1 INDICATIONS AND USAGE

Morphine sulfate extended-release tablets are an opioid agonist indicated for the management of pain severe enough to require daily, around-the-clock, long-term opioid treatment and for which alternative treatment options are inadequate. (1)

Limitations of Use

- Because of the risks of addiction, abuse, and misuse with opioids, even at recommended doses, and because of the greater risks of overdose and death with extended-release opioid formulations, reserve morphine sulfate extended-release tabletsfor use in patients for whom alternative treatment options (e.g., non-opioid analgesics or immediate-release opioids) are ineffective, not tolerated, or would be otherwise inadequate to provide sufficient management of pain. (1)
- Morphine sulfate extended-release tabletsare not indicated as an as-needed (prn) analgesic. (1)

2 DOSAGE AND ADMINISTRATION

- To be prescribed only by healthcare providers knowledgeable in the use of potent opioids for management of chronic pain. (2.1)
- Morphine sulfate extended-release 100 mg and 200 mg tablets, a single dose greater than 60 mg, or a total daily dose greater than 120 mg, are only for use in patients in whom tolerance to an opioid of comparable potency has been established. (2.1)
- Patients considered opioid-tolerant are those taking, for one week or longer, at least 60 mg of morphine per day, 25 mcg transdermal fentanyl per hour, 30 mg of oral oxycodone per day, 8 mg of oral hydromorphone per day, 25 mg oral oxymorphone per day, 60 mg oral hydrocodone per day, or an equianalgesic dose of another opioid. (2.1)
- Use the lowest effective dosage for the shortest duration consistent with individual patient treatment goals. Reserve titration to higher doses of morphine sulfate extended-release tablets for patients in whom lower doses are insufficiently effective and in whom the expected benefits of using a higher dose opioid clearly outweigh the substantial risks. (2.1, 5)
- Individualize dosing based on the severity of pain, patient response, prior analgesic experience, and risk factors for addiction, abuse, and misuse. (2.1)
- Instruct patients to swallow morphine sulfate extended-release tablets intact and not to cut, break, chew, crush, or dissolve morphine sulfate extended-release to avoid the risk of release and absorption of potential fatal dose of morphine. (2.1, 5.1)
- Discuss availability of naloxone with the patient and caregiver and assess each patient’s need for access to naloxone, both when initiating and renewing treatment with morphine sulfate extended-release tablets. Consider prescribing naloxone based on the patient’s risk factors for overdose (2.2, 5.1, 5.3, 5.5).
- For opioid-naïve and opioid non-tolerant patients, initiate with 15 mg tablets orally every 8 to 12 hours. (2.3)
- Do not abruptly discontinue morphine sulfate extended-release tablets in a physically dependent patient because rapid discontinuation of opioid analgesics has resulted in serious withdrawal symptoms, uncontrolled pain, and suicide. (2.5)

3 DOSAGE FORMS AND STRENGTHS

Extended-release tablets: 15 mg, 30 mg, 60 mg, 100 mg, 200 mg (3)

4 CONTRAINDICATIONS

- Significant respiratory depression (4)
- Acute or severe bronchial asthma in an unmonitored setting or in the absence of resuscitative equipment (4)
- Concurrent use of monoamine oxidase inhibitors (MAOIs) or use of MAOIs within the last 14 days (4)
- Known or suspected gastrointestinal obstruction, including paralytic ileus (4)
- Hypersensitivity to morphine (4)

5 WARNINGS AND PRECAUTIONS

- Life-Threatening Respiratory Depression in Patients with Chronic

Pulmonary Disease or in Elderly, Cachectic, or Debilitated Patients: Monitor closely, particularly during initiation and titration. (5.6)

- Adrenal Insufficiency: If diagnosed, treat with physiologic replacement of corticosteroids, and wean patient off of the opioid. (5.8)
- Severe Hypotension: Monitor during dosage initiation and titration. Avoid use in patients with circulatory shock. (5.9)
- Risks of Use in Patients with Increased Intracranial Pressure, Brain Tumors, Head Injury, or Impaired Consciousness: Monitor for sedation and respiratory depression. Avoid use of morphine sulfatein patients with impaired consciousness or coma. (5.10)

6 ADVERSE REACTIONS

Most common adverse reactions (>10%): constipation, nausea, and sedation. (6.1)

To report SUSPECTED ADVERSE REACTIONS, contact Sun Pharmaceutical Industries, Inc. at 1-800-818-4555 or FDA at 1-800-FDA-1088 orwww.fda.gov/medwatch.

7 DRUG INTERACTIONS

- Serotonergic Drugs: Concomitant use may result in serotonin syndrome. Discontinue morphine sulfate if serotonin syndrome is suspected. (7)
- Mixed Agonist/Antagonist and Partial Agonist Opioid Analgesics: Avoid use with morphine sulfate because they may reduce analgesic effect of morphine sulfate or precipitate withdrawal symptoms. (5.13, 7)

8 USE IN SPECIFIC POPULATIONS

- Pregnancy: May cause fetal harm. (8.1)
- Lactation: Not recommended. (8.2)

FULL PRESCRIBING INFORMATION

WARNING: ADDICTION, ABUSE, AND MISUSE; RISK EVALUATION AND MITIGATION STRATEGY (REMS); LIFE-THREATENING RESPIRATORY DEPRESSION; ACCIDENTAL INGESTION; NEONATAL OPIOID WITHDRAWAL SYNDROME; and RISKS FROM CONCOMITANT USE WITH BENZODIAZEPINES OR OTHER CNS DEPRESSANTS

Addiction, Abuse, and Misuse

Morphine sulfate exposes patients and other users to the risks of opioid addiction, abuse, and misuse, which can lead to overdose and death. Assess each patient’s risk prior to prescribing morphine sulfate extended-release tablets, and monitor all patients regularly for the development of these behaviors and conditions [see Warnings and Precautions (5.1)].

Opioid Analgesic Risk Evaluation and Mitigation Strategy (REMS):

To ensure that the benefits of opioid analgesics outweigh the risks of addiction, abuse, and misuse, the Food and Drug Administration (FDA) has required a REMS for these products [see Warnings and Precautions (5.2)]. Under the requirements of the REMS, drug companies with approved opioid analgesic products must make REMS-compliant education programs available to healthcare providers. Healthcare providers are strongly encouraged to:

- complete a REMS-compliant education program,
- counsel patients and/or their caregivers, with every prescription, on safe use, serious risks, storage, and disposal of these products,
- emphasize to patients and their caregivers the importance of reading the Medication Guide every time it is provided by their pharmacist, and
- consider other tools to improve patient, household, and community safety.

Life-Threatening Respiratory Depression

Serious, life-threatening, or fatal respiratory depression may occur with use of morphine sulfate. Monitor for respiratory depression, especially during initiation of morphine sulfate or following a dose increase.Instruct patients to swallow morphine sulfate extended-release tablets whole; crushing, chewing, or dissolving morphine sulfate extended-release tablets can cause rapid release and absorption of a potentially fatal dose of morphine [see Warnings and Precautions (5.3)].

Accidental Ingestion

Accidental ingestion of even one dose of morphine sulfate, especially by children, can result in a fatal overdose of morphine [see Warnings and Precautions (5.3)].

Neonatal Opioid Withdrawal Syndrome (NOWS)

Prolonged use of morphine sulfate during pregnancy can result in neonatal opioid withdrawal syndrome, which may be life-threatening if not recognized and treated, and requires management according to protocols developed by neonatology experts. If opioid use is required for a prolonged period in a pregnant woman, advise the patient of the risk of neonatal opioid withdrawal syndrome and ensure that appropriate treatment will be available [see Warnings and Precautions (5.4)].

Risks From Concomitant Use With Benzodiazepines Or Other CNS Depressants

Concomitant use of opioids with benzodiazepines or other central nervous system (CNS) depressants, including alcohol, may result in profound sedation, respiratory depression, coma, and death [see Warnings and Precautions (5.5), Drug Interactions (7)].

- Reserve concomitant prescribing of morphine sulfate and benzodiazepines or other CNS depressants for use in patients for whom alternative treatment options are inadequate.
- Limit dosages and durations to the minimum required.
- Follow patients for signs and symptoms of respiratory depression and sedation.

1 INDICATIONS AND USAGE

Morphine sulfate extended-release tablets are indicated for the management of pain severe enough to require daily, around-the-clock, long-term opioid treatment and for which alternative treatment options are inadequate.

Limitations of Use

- Because of the risks of addiction, abuse, and misuse with opioids, even at recommended doses, and because of the greater risks of overdose and death with extended-release opioid formulations [see Warnings and Precautions (5.1)], reserve morphine sulfate extended-release tabletsfor use in patients for whom alternative treatment options (e.g., non-opioid analgesics or immediate-release opioids) are ineffective, not tolerated, or would be otherwise inadequate to provide sufficient management of pain.
- Morphine sulfate extended-release tabletsare not indicated as an as-needed (prn) analgesic.

2 DOSAGE AND ADMINISTRATION

2.1 Important Dosage and Administration Instructions

Morphine sulfate extended-release tablets should be prescribed only by healthcare professionals who are knowledgeable in the use of potent opioids for the management of chronic pain.

Morphine sulfate extended-release tablets 100 mg and 200 mg, a single dose greater than 60 mg, or a total daily dose greater than 120 mg, are only for use in patients in whom tolerance to an opioid of comparable potency has been established. Patients considered opioid-tolerant are those taking, for one week or longer, at least 60 mg morphine per day, 25 mcg transdermal fentanyl per hour, 30 mg oral oxycodone per day, 8 mg oral hydromorphone daily, 25 mg oral oxymorphone per day, 60 mg oral hydrocodone per day, or an equianalgesic dose of another opioid.

- Use the lowest effective dosage for the shortest duration consistent with individual patient treatment goals [see Warnings and Precautions (5)].
- Initiate the dosing regimen for each patient individually, taking into account the patient's severity of pain, prior analgesic treatment experience, and risk factors for addiction, abuse, and misuse [see Warnings and Precautions (5.1)].
- Monitor patients closely for respiratory depression, especially within the first 24 to 72 hours of initiating therapy and following dosage increases with morphine sulfate extended-release tablets and adjust the dosage accordingly [see Warnings and Precautions (5.3)].

Instruct patients to swallow morphine sulfate extended-release tablets whole [see Patient Counseling Information (17)]. Crushing, chewing, or dissolving morphine sulfate extended-release tablets will result in uncontrolled delivery of morphine and can lead to overdose or death [see Warnings and Precautions (5.1)].

Morphine sulfate extended-release tablets is administered orally once every 8 or 12 hours.

2.2 Patient Access to Naloxone for the Emergency Treatment of Opioid Overdose

Discuss the availability of naloxone for the emergency treatment of opioid overdose with the patient and caregiver and assess the potential need for access to naloxone, both when initiating and renewing treatment with morphine sulfate extended-release tablets [see Warnings and Precautions (5.3), Patient Counseling Information (17)].

Inform patients and caregivers about the various ways to obtain naloxone as permitted by individual state naloxone dispensing and prescribing requirements or guidelines (e.g., by prescription, directly from a pharmacist, or as part of a community-based program).

Consider prescribing naloxone, based on the patient’s risk factors for overdose, such as concomitant use of CNS depressants, a history of opioid use disorder, or prior opioid overdose. The presence of risk factors for overdose should not prevent the proper management of pain in any given patient [see Warnings and Precautions (5.1, 5.3, 5.5)].

Consider prescribing naloxone if the patient has household members (including children) or other close contacts at risk for accidental ingestion or overdose.

2.3 Initial Dosage

Use of Morphine Sulfate Extended-Release Tablets as the First Opioid Analgesic (opioid-naïve patients)

Initiate treatment with morphine sulfate extended-release tablets with 15 mg tablets orally every 8 or 12 hours.

Use of Morphine Sulfate Extended-Release Tablets in Patients who are not Opioid Tolerant (opioid non-tolerant patients)

The starting dose for patients who are not opioid tolerant is morphine sulfate extended-release tablets 15 mg orally every 12 hours.

Use of higher starting doses in patients who are not opioid tolerant may cause fatal respiratory depression.

Conversion from Other Oral Morphine to Morphine Sulfate Extended-Release Tablets

Patients receiving other oral morphine formulations may be converted to morphine sulfate extended-release tablets by administering one-half of the patient's 24-hour requirement as morphine sulfate extended-release tablets on an every-12-hour schedule or by administering one-third of the patient's daily requirement as morphine sulfate extended-release tablets on an every-8-hour schedule.

Conversion from Other Opioids to Morphine Sulfate Extended-Release Tablets

Discontinue all other around-the-clock opioid drugs when morphine sulfate extended-release tablets therapy is initiated. There are no established conversion ratios for conversion from other opioids to morphine sulfate extended-release tablets defined by clinical trials. Initiate dosing using morphine sulfate extended-release tablets 15 mg orally every 8 to 12 hours.

It is safer to underestimate a patient’s 24-hour oral morphine dosage and provide rescue medication (e.g., immediate-release opioid) than to overestimate the 24-hour oral morphine dosage and manage an adverse reaction due to an overdose. While useful tables of opioid equivalents are readily available, there is inter-patient variability in the potency of opioid drugs and opioid formulations. Close observation and frequent titration are warranted until pain management is stable on the new opioid. Monitor patients for signs and symptoms of opioid withdrawal and for signs of oversedation/toxicity after converting patients to morphine sulfate extended-release tablets.

Conversion from Parenteral Morphine or Other Opioids (Parenteral or Oral) to Morphine Sulfate Extended-Release Tablets

When converting from parenteral morphine or other non-morphine opioids (parenteral or oral) to morphine sulfate extended-release tablets, consider the following general points:

Parenteral to oral morphine ratio: Between 2 to 6 mg of oral morphine may be required to provide analgesia equivalent to 1 mg of parenteral morphine. Typically, a dose of morphine that is approximately three times the previous daily parenteral morphine requirement is sufficient.

Other parenteral or oral non-morphine opioids to oral morphine ratios: Specific recommendations are not available because of a lack of systematic evidence for these types of analgesic substitutions. Published relative potency data are available, but such ratios are approximations. In general, begin with half of the estimated daily morphine requirement as the initial dose, managing inadequate analgesia by supplementation with immediate-release morphine.

Conversion from Methadone to Morphine Sulfate Extended-Release Tablets

Close monitoring is of particular importance when converting methadone to other opioid agonists. The ratio between methadone and other opioid agonists may vary widely as a function of previous dose exposure. Methadone has a long half-life and can accumulate in the plasma.

2.4 Titration and Maintenance of Therapy

Individually titrate morphine sulfate extended-release tablets to a dose that provides adequate analgesia and minimizes adverse reactions. Continually reevaluate patients receiving morphine sulfate extended-release tablets to assess the maintenance of pain control, signs and symptoms of opioid withdrawal, and other adverse reactions, as well as to reassess for the development of addiction, abuse, or misuse [see Warnings and Precautions (5.1)]. Frequent communication is important among the prescriber, other members of the healthcare team, the patient, and the caregiver/family during periods of changing analgesic requirements, including initial titration. During chronic therapy periodically reassess the continued need for the use of opioid analgesics.

Patients who experience breakthrough pain may require a dosage adjustment of morphine sulfate extended-release tablets, or may need rescue medication with an appropriate dose of an immediate-release analgesic. If the level of pain increases after dose stabilization, attempt to identify the source of increased pain before increasing the morphine sulfate extended-release tablets dosage. Because steady-state plasma concentrations are approximated in 1 day, morphine sulfate extended-release tablets dosage adjustments may be done every 1 to 2 days.

If after increasing the dosage, unacceptable opioid-related adverse reactions are observed (including an increase in pain after dosage increase), consider reducing the dosage [see Warnings and Precautions (5)]. Adjust the dosage to obtain an appropriate balance between management of pain and opioid-related adverse reactions.

2.5 Dosage Modifications with Concomitant Use of Central Nervous System Depressants

If the patient is currently taking a central nervous system (CNS) depressant and the decision is made to begin morphine sulfate, start with the lowest possible dose, 15 mg every 12 hours, monitor patients for signs of respiratory depression, sedation, and hypotension, and consider using a lower dosage of the concomitant CNS depressant [see Warnings and Precautions (5.5), Drug Interactions (7)].

2.6 Safe Reduction or Discontinuation of Morphine Sulfate Extended-Release Tablets

Do not abruptly discontinue morphine sulfate extended-release tablets in patients who may be physically dependent on opioids. Rapid discontinuation of opioid analgesics in patients who are physically dependent on opioids has resulted in serious withdrawal symptoms, uncontrolled pain, and suicide. Rapid discontinuation has also been associated with attempts to find other sources of opioid analgesics, which may be confused with drug-seeking for abuse. Patients may also attempt to treat their pain or withdrawal symptoms with illicit opioids, such as heroin, and other substances.

When a decision has been made to decrease the dose or discontinue therapy in an opioid-dependent patient taking morphine sulfate extended-release tablets, there are a variety of factors that should be considered, including the total daily dose of opioid (including morphine sulfate extended-release tablets) the patient has been taking, the duration of treatment, the type of pain being treated, and the physical and psychological attributes of the patient. It is important to ensure ongoing care of the patient and to agree on an appropriate tapering schedule and follow-up plan so that patient and provider goals and expectations are clear and realistic. When opioid analgesics are being discontinued due to a suspected substance use disorder, evaluate and treat the patient, or refer for evaluation and treatment of the substance use disorder. Treatment should include evidence-based approaches, such as medication assisted treatment of opioid use disorder. Complex patients with co-morbid pain and substance use disorders may benefit from referral to a specialist.

There are no standard opioid tapering schedules that are suitable for all patients. Good clinical practice dictates a patient-specific plan to taper the dose of the opioid gradually. For patients on morphine sulfate extended-release tablets who are physically opioid-dependent, initiate the taper by a small enough increment (e.g., no greater than 10% to 25% of the total daily dose) to avoid withdrawal symptoms, and proceed with dose-lowering at an interval of every 2 to 4 weeks. Patients who have been taking opioids for briefer periods of time may tolerate a more rapid taper.

It may be necessary to provide the patient with lower dosage strengths to accomplish a successful taper. Reassess the patient frequently to manage pain and withdrawal symptoms, should they emerge. Common withdrawal symptoms include restlessness, lacrimation, rhinorrhea, yawning, perspiration, chills, myalgia, and mydriasis. Other signs and symptoms also may develop, including irritability, anxiety, backache, joint pain, weakness, abdominal cramps, insomnia, nausea, anorexia, vomiting, diarrhea, or increased blood pressure, respiratory rate, or heart rate. If withdrawal symptoms arise, it may be necessary to pause the taper for a period of time or raise the dose of the opioid analgesic to the previous dose, and then proceed with a slower taper. In addition, monitor patients for any changes in mood, emergence of suicidal thoughts, or use of other substances.

When managing patients taking opioid analgesics, particularly those who have been treated for a long duration and/or with high doses for chronic pain, ensure that a multimodal approach to pain management, including mental health support (if needed), is in place prior to initiating an opioid analgesic taper. A multimodal approach to pain management may optimize the treatment of chronic pain, as well as assist with the successful tapering of the opioid analgesic [see Warnings and Precautions (5.13), Drug Abuse and Dependence (9.3)].

3 DOSAGE FORMS AND STRENGTHS

- · Morphine sulfate extended-release tablets 15 mg
  Round, blue-colored, film-coated tablets debossed with “RD” and “70” on one side and plain on the other side
- Morphine sulfate extended-release tablets 30 mg
  Round, purple-colored, film-coated tablets debossed with “RD” and “71” on one side and plain on the other side
- Morphine sulfate extended-release tablets 60 mg
  Round, light orange-colored, film-coated tablets debossed with “RD” and “72” on one side and plain on the other side
- Morphine sulfate extended-release tablets 100 mg*
  Round, gray-colored, film-coated tablets debossed with “RD” and “73” on one side and plain on the other side
- Morphine sulfate extended-release tablets 200 mg*
  Oval, green-colored, film-coated tablets debossed with “RD74” on one side and plain on the other side

*100 mg and 200 mg tablets are for use in opioid-tolerant patients only

4 CONTRAINDICATIONS

Morphine sulfate is contraindicated in patients with:

- Significant respiratory depression [see Warnings and Precautions (5.3)]
- Acute or severe bronchial asthma in an unmonitored setting or in the absence of resuscitative equipment [see Warnings and Precautions (5.6)]
- Concurrent use of monoamine oxidase inhibitors (MAOIs) or use of MAOIs within the last 14 days [see Warnings and Precautions (5.7), Drug Interactions (7)].
- Hypersensitivity (e.g., anaphylaxis) to morphine [see Adverse Reactions (6.2)]

- Known or suspected gastrointestinal obstruction, including paralytic ileus [see Warnings and Precautions (5.11)]

5 WARNINGS AND PRECAUTIONS

5.1 Addiction, Abuse, and Misuse

Morphine sulfate extended-release tablets contain morphine, a Schedule II controlled substance. As an opioid, morphine sulfate exposes its users to the risks of addiction, abuse, and misuse. Because extended-release products such as morphine sulfatedeliver the opioid over an extended period of time, there is a greater risk for overdose and death due to the larger amount of morphine present [see Drug Abuse and Dependence (9)].

Although the risk of addiction in any individual is unknown, it can occur in patients appropriately prescribed morphine sulfate. Addiction can occur at recommended doses and if the drug is misused or abused.

Assess each patient’s risk for opioid addiction, abuse, or misuse prior to prescribing morphine sulfate, and monitor all patients receiving morphine sulfate for development of these behaviors and conditions. Risks are increased in patients with a personal or family history of substance abuse (including drug or alcohol abuse or addiction) or mental illness (e.g., major depression). The potential for these risks should not, however, prevent the proper management of pain in any given patient. Patients at increased risk may be prescribed opioids such as morphine sulfate, but use in such patients necessitates intensive counseling about the risks of proper use of morphine sulfate along with intensive monitoring for signs of addiction, abuse, and misuse. Consider prescribing naloxone for the emergency treatment of opioid overdose [see Dosage and Administration (2.2), Warnings and Precautions (5.3)].

Abuse or misuse of morphine sulfate extended-release tablets by crushing, chewing, snorting, or injecting the dissolved product will result in the uncontrolled delivery of morphine and can result in overdose and death [see Overdosage (10)].

Opioids are sought for nonmedical use and are subject to diversion from legitimate prescribed use. Consider these risks when prescribing or dispensing morphine sulfate. Strategies to reduce these risks include prescribing the drug in the smallest appropriate quantity and advising the patient on careful storage of the drug during the course of treatment and proper disposal of unused drug. Contact local state professional licensing board or state-controlled substances authority for information on how to prevent and detect abuse or diversion of this product.

5.2 Opioid Analgesic Risk Evaluation and Mitigation Strategy (REMS)

To ensure that the benefits of opioid analgesics outweigh the risks of addiction, abuse, and misuse, the Food and Drug Administration (FDA) has required a Risk Evaluation and Mitigation Strategy (REMS) for these products. Under the requirements of the REMS, drug companies with approved opioid analgesic products must make REMS-compliant education programs available to healthcare providers. Healthcare providers are strongly encouraged to do all of the following:

- Complete a REMS-compliant education program offered by an accredited provider of continuing education (CE) or another education program that includes all the elements of the FDA Education Blueprint for Health Care Providers Involved in the Management or Support of Patients with Pain.
- Discuss the safe use, serious risks, and proper storage and disposal of opioid analgesics with patients and/or their caregivers every time these medicines are prescribed. The Patient Counseling Guide (PCG) can be obtained at this link: http://www.fda.gov/OpioidAnalgesicREMSPCG.
- Emphasize to patients and their caregivers the importance of reading the Medication Guide that they will receive from their pharmacist every time an opioid analgesic is dispensed to them.
- Consider using other tools to improve patient, household, and community safety, such as patient-prescriber agreements that reinforce patient-prescriber responsibilities.

To obtain further information on the opioid analgesic REMS and for a list of accredited REMS CME/CE, call 1-800-503-0784, or log on to www.opioidanalgesicrems.com. The FDA Blueprint can be found at www.fda.gov/OpioidAnalgesicREMSBlueprint.

5.3 Life-Threatening Respiratory Depression

Serious, life-threatening, or fatal respiratory depression has been reported with the use of opioids, even when used as recommended. Respiratory depression, if not immediately recognized and treated, may lead to respiratory arrest and death. Management of respiratory depression may include close observation, supportive measures, and use of opioid antagonists, depending on the patient’s clinical status [see Overdosage (10)]. Carbon dioxide (CO2) retention from opioid-induced respiratory depression can exacerbate the sedating effects of opioids.

While serious, life-threatening, or fatal respiratory depression can occur at any time during the use of morphine sulfate, the risk is greatest during the initiation of therapy or following a dosage increase. Monitor patients closely for respiratory depression especially within the first 24 to 72 hours of initiating therapy and following dosage increases of morphine sulfate.

To reduce the risk of respiratory depression, proper dosing and titration of morphine sulfate are essential [see Dosage and Administration (2)]. Overestimating the morphine sulfate dosage when converting patients from another opioid product can result in a fatal overdose with the first dose.

Accidental ingestion of even one dose of morphine sulfate, especially by children, can result in respiratory depression and death due to an overdose of morphine.

Educate patients and caregivers on how to recognize respiratory depression and emphasize the importance of calling 911 or getting emergency medical help right away in the event of a known or suspected overdose [see Patient Counseling Information (17)].

Opioids can cause sleep-related breathing disorders including central sleep apnea (CSA) and sleep-related hypoxemia. Opioid use increases the risk of CSA in a dose-dependent fashion. In patients who present with CSA, consider decreasing the opioid dosage using best practices for opioid taper [see Dosage and Administration (2.6)].

Patient Access to Naloxone for the Emergency Treatment of Opioid Overdose:

Discuss the availability of naloxone for the emergency treatment of opioid overdose with the patient and caregiver and assess the potential need for access to naloxone, both when initiating and renewing treatment with morphine sulfate. Inform patients and caregivers about the various ways to obtain naloxone as permitted by individual state naloxone dispensing and prescribing requirements or guidelines (e.g., by prescription, directly from a pharmacist, or as part of a community-based program). Educate patients and caregivers on how to recognize respiratory depression and emphasize the importance of calling 911 or getting emergency medical help, even if naloxone is administered [see Patient Counseling Information (17)].

Consider prescribing naloxone, based on the patient’s risk factors for overdose, such as concomitant use of CNS depressants, a history of opioid use disorder, or prior opioid overdose. The presence of risk factors for overdose should not prevent the proper management of pain in any given patient. Also consider prescribing naloxone if the patient has household members (including children) or other close contacts at risk for accidental ingestion or overdose. If naloxone is prescribed, educate patients and caregivers on how to treat with naloxone. [see Warnings and Precautions (5.1, 5.5), Patient Counseling Information (17)].

5.4 Neonatal Opioid Withdrawal Syndrome

Prolonged use of morphine sulfate during pregnancy can result in withdrawal in the neonate. Neonatal opioid withdrawal syndrome, unlike opioid withdrawal syndrome in adults, may be life-threatening if not recognized and treated, and requires management according to protocols developed by neonatology experts. Observe newborns for signs of neonatal opioid withdrawal syndrome and manage accordingly. Advise pregnant women using opioids for a prolonged period of the risk of neonatal opioid withdrawal syndrome and ensure that appropriate treatment will be available [see Use in Specific Populations (8.1), Patient Counseling Information (17)].

5.5 Risks from Concomitant Use with Benzodiazepines or Other CNS Depressants

Profound sedation, respiratory depression, coma, and death may result from the concomitant use of morphine sulfate with benzodiazepines and/or other CNS depressants, including alcohol (e.g., non-benzodiazepine sedatives/hypnotics, anxiolytics, tranquilizers, muscle relaxants, general anesthetics, antipsychotics, other opioids, alcohol). Because of these risks, reserve concomitant prescribing of these drugs for use in patients for whom alternative treatment options are inadequate.
Observational studies have demonstrated that concomitant use of opioid analgesics and benzodiazepines increases the risk of drug-related mortality compared to use of opioid analgesics alone. Because of similar pharmacological properties, it is reasonable to expect similar risk with the concomitant use of other CNS depressant drugs with opioid analgesics [see Drug Interactions (7)].
If the decision is made to prescribe a benzodiazepine or other CNS depressant concomitantly with an opioid analgesic, prescribe the lowest effective dosages and minimum durations of concomitant use. In patients already receiving an opioid analgesic, prescribe a lower initial dose of the benzodiazepine or other CNS depressant than indicated in the absence of an opioid, and titrate based on clinical response. If an opioid analgesic is initiated in a patient already taking a benzodiazepine or other CNS depressant, prescribe a lower initial dose of the opioid analgesic, and titrate based on clinical response. Follow patients closely for signs and symptoms of respiratory depression and sedation.
If concomitant use is warranted, consider prescribing naloxone for the emergency treatment of opioid overdose [see Dosage and Administration (2.2), Warnings and Precautions (5.3)].
Advise both patients and caregivers about the risks of respiratory depression and sedation when morphine sulfate is used with benzodiazepines or other CNS depressants (including alcohol and illicit drugs). Advise patients not to drive or operate heavy machinery until the effects of concomitant use of the benzodiazepine or other CNS depressant have been determined. Screen patients for risk of substance use disorders, including opioid abuse and misuse, and warn them of the risk for overdose and death associated with the use of additional CNS depressants including alcohol and illicit drugs [see Drug Interactions (7), Patient Counseling Information (17)].

5.6 Risk of Life-Threatening Respiratory Depression in Patients with Chronic Pulmonary Disease or in Elderly, Cachectic, or Debilitated Patients

The use of morphine sulfate in patients with acute or severe bronchial asthma in an unmonitored setting or in the absence of resuscitative equipment is contraindicated.

Patients with Chronic Pulmonary Disease: Morphine sulfate -treated patients with significant chronic obstructive pulmonary disease or cor pulmonale, and those with a substantially decreased respiratory reserve, hypoxia, hypercapnia, or pre-existing respiratory depression are at increased risk of decreased respiratory drive including apnea, even at recommended dosages of morphine sulfate [see Warnings and Precautions (5.3)].

Elderly, Cachectic, or Debilitated Patients: Life-threatening respiratory depression is more likely to occur in elderly, cachectic, or debilitated patients as they may have altered pharmacokinetics or altered clearance compared to younger, healthier patients [see Warnings and Precautions (5.3)].

Monitor such patients closely, particularly when initiating and titrating morphine sulfate and when morphine sulfate is given concomitantly with other drugs that depress respiration [see Warnings and Precautions (5.3)]. Alternatively, consider the use of non-opioid analgesics in these patients.

5.7 Interaction with Monoamine Oxidase Inhibitors

Monoamine oxidase inhibitors (MAOIs) may potentiate the effects of morphine, including respiratory depression, coma, and confusion. Morphine sulfate should not be used in patients taking MAOIs or within 14 days of stopping such treatment.

5.8 Adrenal Insufficiency

Cases of adrenal insufficiency have been reported with opioid use, more often following greater than one month of use. Presentation of adrenal insufficiency may include non-specific symptoms and signs including nausea, vomiting, anorexia, fatigue, weakness, dizziness, and low blood pressure. If adrenal insufficiency is suspected, confirm the diagnosis with diagnostic testing as soon as possible. If adrenal insufficiency is diagnosed, treat with physiologic replacement doses of corticosteroids. Wean the patient off of the opioid to allow adrenal function to recover and continue corticosteroid treatment until adrenal function recovers. Other opioids may be tried as some cases reported use of a different opioid without recurrence of adrenal insufficiency. The information available does not identify any particular opioids as being more likely to be associated with adrenal insufficiency.

5.9 Severe Hypotension

Morphine sulfate may cause severe hypotension including orthostatic hypotension and syncope in ambulatory patients. There is increased risk in patients whose ability to maintain blood pressure has already been compromised by a reduced blood volume or concurrent administration of certain CNS depressant drugs (e.g., phenothiazines or general anesthetics) [see Drug Interactions (7)]. Monitor these patients for signs of hypotension after initiating or titrating the dosage of morphinesulfate. In patients with circulatory shock, morphine sulfate may cause vasodilation that can further reduce cardiac output and blood pressure. Avoid the use of morphine sulfate in patients with circulatory shock.

5.10 Risks of Use in Patients with Increased Intracranial Pressure, Brain Tumors, Head Injury, or Impaired Consciousness

In patients who may be susceptible to the intracranial effects of CO2 retention (e.g., those with evidence of increased intracranial pressure or brain tumors), morphine sulfate may reduce respiratory drive, and the resultant CO2 retention can further increase intracranial pressure. Monitor such patients for signs of sedation and respiratory depression, particularly when initiating therapy with morphine sulfate.

Opioids may also obscure the clinical course in a patient with a head injury. Avoid the use of morphine sulfate in patients with impaired consciousness or coma.

5.11 Risks of Use in Patients with Gastrointestinal Conditions

Morphine sulfate is contraindicated in patients with known or suspected gastrointestinal obstruction, including paralytic ileus.

The morphine in morphine sulfate may cause spasm of the sphincter of Oddi. Opioids may cause increases in serum amylase. Monitor patients with biliary tract disease, including acute pancreatitis, for worsening symptoms.

5.12 Increased Risk of Seizures in Patients with Seizure Disorders

The morphine in morphine sulfate may increase the frequency of seizures in patients with seizure disorders, and may increase the risk of seizures occurring in other clinical settings associated with seizures. Monitor patients with a history of seizure disorders for worsened seizure control during morphine sulfate therapy.

5.13 Withdrawal

Do not abruptly discontinue morphine sulfate in a patient physically dependent on opioids. When discontinuing morphine sulfate in a physically dependent patient, gradually taper the dosage. Rapid tapering of morphine in a patient physically dependent on opioids may lead to a withdrawal syndrome and return of pain [see Dosage and Administration (2.5), Drug Abuse and Dependence (9.3)].

Additionally, avoid the use of mixed agonist/antagonist (e.g., pentazocine, nalbuphine, and butorphanol) or partial agonist (e.g., buprenorphine) analgesics in patients who have received or are receiving a course of therapy with a full opioid agonist analgesic, including morphine sulfate. In these patients, mixed agonists/antagonist and partial agonist analgesics may reduce the analgesic effect and/or may precipitate withdrawal symptoms [see Drug Interactions (7)].

5.14 Risks of Driving and Operating Machinery

Morphine sulfate may impair the mental or physical abilities needed to perform potentially hazardous activities such as driving a car or operating machinery. Warn patients not to drive or operate dangerous machinery unless they are tolerant to the effects of morphine sulfate and know how they will react to the medication [see Patient Counseling Information (17)].

6 ADVERSE REACTIONS

The following serious adverse reactions are described, or described in greater detail, in other sections:

- Addiction, Abuse, and Misuse [see Warnings and Precautions (5.1)]
- Life-Threatening Respiratory Depression [see Warnings and Precautions (5.3)]
- Neonatal Opioid Withdrawal Syndrome [see Warnings and Precautions (5.4)]
- Interactions with Benzodiazepine or Other CNS Depressants [see Warnings and Precautions (5.5)]
- Adrenal Insufficiency [see Warnings and Precautions (5.8)]
- Severe Hypotension [see Warnings and Precautions (5.9)]
- Gastrointestinal Adverse Reactions [see Warnings and Precautions (5.11)]
- Seizures [see Warnings and Precautions (5.12)]
- Withdrawal [see Warnings and Precautions (5.13)]

6.1 Clinical Trial Experience

Because clinical trials are conducted under widely varying conditions, adverse reaction rates observed in the clinical trials of a drug cannot be directly compared to rates in the clinical trials of another drug and may not reflect the rates observed in practice.

Morphine sulfate may increase the risk of serious adverse reactions such as those observed with other opioid analgesics, including respiratory depression, apnea, respiratory arrest, circulatory depression, hypotension, or shock [see Overdosage (10)].

Most Frequently Observed Reactions

In clinical trials, the most common adverse reactions with morphine sulfate were constipation, dizziness, sedation, nausea, vomiting, sweating, dysphoria, and euphoric mood.

Some of these effects seem to be more prominent in ambulatory patients and in those not experiencing severe pain.

Less Frequently Observed Reactions

Cardiovascular disorders: tachycardia, bradycardia, palpitations

Eye disorders: visual impairment, vision blurred, diplopia, miosis

Gastrointestinal disorders: dry mouth, diarrhea, abdominal pain, constipation, dyspepsia

General disorders and administration site conditions: chills, feeling abnormal, edema, edema peripheral, weakness

Hepatobiliary disorders: biliary colic

Metabolism and nutrition disorders: anorexia

Musculoskeletal and connective tissue disorders: muscle rigidity, muscle twitching

Nervous system disorders: presyncope, syncope, headache, tremor, uncoordinated muscle movements, convulsion, intracranial pressure increased, taste alteration, paresthesia, nystagmus

Psychiatric disorders: agitation, mood altered, anxiety, depression, abnormal dreams, hallucination, disorientation, insomnia

Renal and urinary disorders: urinary retention, urinary hesitation, antidiuretic effects

Reproductive system and breast disorders: reduced libido and/or potency

Respiratory, thoracic and mediastinal disorders: laryngospasm

Skin and subcutaneous tissue disorders: pruritus, urticaria, rash

Vascular disorders: flushing, hypotension, hypertension

6.2 Post-Marketing Experience

The following adverse reactions have been identified during post-approval use of morphine sulfate. Because these reactions are reported voluntarily from a population of uncertain size, it is not always possible to reliably estimate their frequency or establish a causal relationship to drug exposure.

Amenorrhea, asthenia, bronchospasm, confusional state, drug hypersensitivity, fatigue, hyperalgesia, hypertonia, ileus, increased hepatic enzymes, intestinal obstruction, lethargy, malaise, pulmonary edema, thinking disturbances, somnolence, and vertigo.

Serotonin syndrome: Cases of serotonin syndrome, a potentially life-threatening condition, have been reported during concomitant use of opioids with serotonergic drugs.

Adrenal insufficiency: Cases of adrenal insufficiency have been reported with opioid use, more often following greater than one month of use.

Anaphylaxis: Anaphylaxis has been reported with ingredients contained in morphine sulfate.

Androgen deficiency: Cases of androgen deficiency have occurred with chronic use of opioids [see Clinical Pharmacology (12.2)].

7 DRUG INTERACTIONS

Table 1 includes clinically significant drug interactions with morphine sulfate.

Table 1: Clinically Significant Drug Interactions with morphine sulfate

Benzodiazepines and Other Central Nervous System (CNS) Depressants
Clinical Impact: | Due to additive pharmacologic effect, the concomitant use of benzodiazepines or other CNS depressants, including alcohol, can increase the risk of hypotension, respiratory depression, profound sedation, coma, and death.
Intervention: | Reserve concomitant prescribing of these drugs for use in patients for whom alternative treatment options are inadequate. Limit dosages and durations to the minimum required. Follow patients closely for signs of respiratory depression and sedation. If concomitant use is warranted, consider prescribing naloxone for the emergency treatment of opioid overdose [see Dosage and Administration (2.2, 2.5), Warnings and Precautions (5.1, 5.3, 5.5)].
Examples: | Benzodiazepines and other sedative hypnotics, anxiolytics, tranquilizers, muscle relaxants, general anesthetics, antipsychotics, other opioids, alcohol.
Serotonergic Drugs
Clinical Impact: | The concomitant use of opioids with other drugs that affect the serotonergic neurotransmitter system has resulted in serotonin syndrome.
Intervention: | If concomitant use is warranted, carefully observe the patient, particularly during treatment initiation and dose adjustment. Discontinue morphine sulfate if serotonin syndrome is suspected.
Examples: | Selective serotonin reuptake inhibitors (SSRIs), serotonin and norepinephrine reuptake inhibitors (SNRIs), tricyclic antidepressants (TCAs), triptans, 5-HT3 receptor antagonists, drugs that effect the serotonin neurotransmitter system (e.g., mirtazapine, trazodone, tramadol), certain muscle relaxants (i.e., cyclobenzaprine, metaxalone), monoamine oxidase (MAO) inhibitors (those intended to treat psychiatric disorders and also others, such as linezolid and intravenous methylene blue).
Monoamine Oxidase Inhibitors (MAOIs)
Clinical Impact: | MAOI interactions with opioids may manifest as serotonin syndrome or opioid toxicity (e.g., respiratory depression, coma) [see Warnings and Precautions (5.7)].
Intervention: | Do not use morphine sulfate in patients taking MAOIs or within 14 days of stopping such treatment.
Examples: | phenelzine, tranylcypromine, linezolid
Mixed Agonist/Antagonist and Partial Agonist Opioid Analgesics
Clinical Impact: | May reduce the analgesic effect of morphine sulfate and/or precipitate withdrawal symptoms.
Intervention: | Avoid concomitant use.
Examples: | butorphanol, nalbuphine, pentazocine, buprenorphine
Muscle Relaxants
Clinical Impact: | Morphine may enhance the neuromuscular blocking action of skeletal muscle relaxants and produce an increased degree of respiratory depression.
Intervention: | Evaluate patients for signs of respiratory depression that may be greater than otherwise expected and decrease the dosage of morphine sulfate and/or the muscle relaxant as necessary. Due to the risk of respiratory depression with concomitant use of skeletal muscle relaxants and opioids, consider prescribing naloxone for the emergency treatment of opioid overdose [see Dosage and Administration (2.2), Warnings and Precautions (5.3, 5.5)]
Examples: | Cyclobenzaprine, metaxalone
Cimetidine
Clinical Impact: | The concomitant use of cimetidine can potentiate morphine effects and increase risk of hypotension, respiratory depression, profound sedation, coma, and death.
Intervention: | Evaluate patients for signs of respiratory depression that may be greater than otherwise expected and decrease the dosage of morphine sulfate and/or cimetidine as necessary.
Diuretics
Clinical Impact: | Opioids can reduce the efficacy of diuretics by inducing the release of antidiuretic hormone.
Intervention: | Evaluate patients for signs of diminished diuresis and/or effects on blood pressure and increase the dosage of the diuretic as needed.
Anticholinergic Drugs
Clinical Impact: | The concomitant use of anticholinergic drugs may increase risk of urinary retention and/or severe constipation, which may lead to paralytic ileus.
Intervention: | Evaluate patients for signs of urinary retention or reduced gastric motility when morphine sulfate is used concomitantly with anticholinergic drugs.
P-Glycoprotein (P-gp) Inhibitors
Clinical Impact: | The concomitant use of PGP-inhibitors can increase the exposure to morphine by about two-fold and can increase risk of hypotension, respiratory depression, profound sedation, coma, and death.
Intervention: | Evaluate patients for signs of respiratory depression that may be greater than otherwise expected and decrease the dosage of morphine sulfate and/or the PGP-inhibitor as necessary.
Example: | Quinidine

8 USE IN SPECIFIC POPULATIONS

8.1 Pregnancy

Risk Summary

Prolonged use of opioid analgesics during pregnancy may cause neonatal withdrawal syndrome [see Warnings and Precautions (5.4)]. There are no available data with morphine sulfate in pregnant women to inform a drug-associated risk for major birth defects and miscarriage. Published studies with morphine use during pregnancy have not reported a clear association with morphine and major birth defects [see Human Data]. In published animal reproduction studies, morphine administered subcutaneously during the early gestational period produced neural tube defects (i.e., exencephaly and cranioschisis) at 5 and 16 times the human daily dose of 60 mg based on body surface area (HDD) in hamsters and mice, respectively, lower fetal body weight and increased incidence of abortion at 0.4 times the HDD in the rabbit, growth retardation at 6 times the HDD in the rat, and axial skeletal fusion and cryptorchidism at 16 times the HDD in the mouse. Administration of morphine sulfate to pregnant rats during organogenesis and through lactation resulted in cyanosis, hypothermia, decreased brain weights, pup mortality, decreased pup body weights, and adverse effects on reproductive tissues at 3 to 4 times the HDD; and long-term neurochemical changes in the brain of offspring which correlate with altered behavioral responses that persist through adulthood at exposures comparable to and less than the HDD [see Animal Data]. Based on animal data, advise pregnant women of the potential risk to a fetus. The estimated background risk of major birth defects and miscarriage for the indicated population is unknown. All pregnancies have a background risk of birth defect, loss, or other adverse outcomes. In the U.S. general population, the estimated background risk of major birth defects and miscarriage in clinically recognized pregnancies is 2 to 4% and 15 to 20%, respectively.

Clinical Considerations

Fetal/Neonatal Adverse Reactions

Prolonged use of opioid analgesics during pregnancy for medical or nonmedical purposes can result in physical dependence in the neonate and neonatal opioid withdrawal syndrome shortly after birth. Neonatal opioid withdrawal syndrome presents as irritability, hyperactivity and abnormal sleep pattern, high pitched cry, tremor, vomiting, diarrhea, and failure to gain weight. The onset, duration, and severity of neonatal opioid withdrawal syndrome vary based on the specific opioid used, duration of use, timing and amount of last maternal use, and rate of elimination of the drug by the newborn. Observe newborns for symptoms of neonatal opioid withdrawal syndrome and manage accordingly [see Warnings and Precautions (5.4)].

Labor or Delivery

Opioids cross the placenta and may produce respiratory depression and psycho-physiologic effects in neonates. An opioid antagonist, such as naloxone, must be available for reversal of opioid-induced respiratory depression in the neonate. Morphine sulfate is not recommended for use in pregnant women during or immediately prior to labor, when use of shorter-acting analgesics or other analgesic techniques are more appropriate. Opioid analgesics, including morphine sulfate, can prolong labor through actions which temporarily reduce the strength, duration, and frequency of uterine contractions. However, this effect is not consistent and may be offset by an increased rate of cervical dilation, which tends to shorten labor. Monitor neonates exposed to opioid analgesics during labor for signs of excess sedation and respiratory depression.

Data

Human Data

The results from a population-based prospective cohort, including 70 women exposed to morphine during the first trimester of pregnancy and 448 women exposed to morphine at any time during pregnancy, indicate no increased risk for congenital malformations. However, these studies cannot definitely establish the absence of any risk because of methodological limitations, including small sample size and non-randomized study design.

Animal Data

Formal reproductive and developmental toxicology studies for morphine have not been conducted. Exposure margins for the following published study reports are based on human daily dose of 60 mg morphine using a body surface area comparison (HDD).

Neural tube defects (exencephaly and cranioschisis) were noted following subcutaneous administration of morphine sulfate (35-322 mg/kg) on Gestation Day 8 to pregnant hamsters (4.7 to 43.5 times the HDD). A no adverse effect level was not defined in this study and the findings cannot be clearly attributed to maternal toxicity. Neural tube defects (exencephaly), axial skeletal fusions, and cryptorchidism were reported following a single subcutaneous (SC) injection of morphine sulfate to pregnant mice (100-500 mg/kg) on Gestation Day 8 or 9 at 200 mg/kg or greater (16 times the HDD) and fetal resorption at 400 mg/kg or higher (32 times the HDD). No adverse effects were noted following 100 mg/kg morphine in this model (8 times the HDD). In one study, following continuous subcutaneous infusion of doses greater than or equal to 2.72 mg/kg to mice (0.2 times the HDD), exencephaly, hydronephrosis, intestinal hemorrhage, split supraoccipital, malformed sternebrae, and malformed xiphoid were noted. The effects were reduced with increasing daily dose; possibly due to rapid induction of tolerance under these infusion conditions. The clinical significance of this report is not clear.

Decreased fetal weights were observed in pregnant rats treated with 20 mg/kg/day morphine sulfate (3.2 times the HDD) from Gestation Day 7 to 9. There was no evidence of malformations despite maternal toxicity (10% mortality). In a second rat study, decreased fetal weight and increased incidences of growth retardation were noted at 35 mg/kg/day (5.7 times the HDD) and there was a reduced number of fetuses at 70 mg/kg/day (11.4 times the HDD) when pregnant rats were treated with 10, 35, or 70 mg/kg/day morphine sulfate via continuous infusion from Gestation Day 5 to 20. There was no evidence of fetal malformations or maternal toxicity.

An increased incidence of abortion was noted in a study in which pregnant rabbits were treated with 2.5 (0.8 times the HDD) to 10 mg/kg morphine sulfate via subcutaneous injection from Gestation Day 6 to 10. In a second study, decreased fetal body weights were reported following treatment of pregnant rabbits with increasing doses of morphine (10-50 mg/kg/day) during the pre-mating period and 50 mg/kg/day (16 times the HDD) throughout the gestation period. No overt malformations were reported in either publication; although only limited endpoints were evaluated.

In published studies in rats, exposure to morphine during gestation and/or lactation periods is associated with: decreased pup viability at 12.5 mg/kg/day or greater (2 times the HDD); decreased pup body weights at 15 mg/kg/day or greater (2.4 times the HDD); decreased litter size, decreased absolute brain and cerebellar weights, cyanosis, and hypothermia at 20 mg/kg/day (3.2 times the HDD); alteration of behavioral responses (play, social-interaction) at 1 mg/kg/day or greater (0.2 times the HDD); alteration of maternal behaviors (e.g., decreased nursing and pup retrievals) in mice at 1 mg/kg or higher (0.08 times the HDD) and rats at 1.5 mg/kg/day or higher (0.2 times the HDD); and a host of behavioral abnormalities in the offspring of rats, including altered responsiveness to opioids at 4 mg/kg/day (0.7 times the HDD) or greater.

Fetal and/or postnatal exposure to morphine in mice and rats has been shown to result in morphological changes in fetal and neonatal brain and neuronal cell loss, alteration of a number of neurotransmitter and neuromodulator systems, including opioid and non-opioid systems, and impairment in various learning and memory tests that appear to persist into adulthood. These studies were conducted with morphine treatment usually in the range of 4 to 20 mg/kg/day (0.7 to 3.2 times the HDD).

Additionally, delayed sexual maturation and decreased sexual behaviors in female offspring at 20 mg/kg/day (3.2 times the HDD), and decreased plasma and testicular levels of luteinizing hormone and testosterone, decreased testes weights, seminiferous tubule shrinkage, germinal cell aplasia, and decreased spermatogenesis in male offspring were also observed at 20 mg/kg/day (3.2 times the HDD). Decreased litter size and viability were observed in the offspring of male rats that were intraperitoneally administered morphine sulfate for 1 day prior to mating at 25 mg/kg/day (4.1 times the HDD) and mated to untreated females. Decreased viability and body weight and/or movement deficits in both first and second generation offspring were reported when male mice were treated for 5 days with escalating doses of 120 to 240 mg/kg/day morphine sulfate (9.7 to 19.5 times the HDD) or when female mice treated with escalating doses of 60 to 240 mg/kg/day (4.9 to 19.5 times the HDD) followed by a 5-day treatment-free recovery period prior to mating. Similar multigenerational findings were also seen in female rats pre-gestationally treated with escalating doses of 10 to 22 mg/kg/day morphine (1.6 to 3.6 times the HDD).

8.2 Lactation

Risk Summary

Morphine is present in breast milk. Published lactation studies report variable concentrations of morphine in breast milk with administration of immediate-release morphine to nursing mothers in the early postpartum period with a milk-to-plasma morphine AUC ratio of 2.5:1 measured in one lactation study. However, there is insufficient information to determine the effects of morphine on the breastfed infant and the effects of morphine on milk production. Lactation studies have not been conducted with extended-release morphine, including morphine sulfate. Because of the potential for serious adverse reactions, including excess sedation and respiratory depression in a breastfed infant, advise patients that breastfeeding is not recommended during treatment with morphine sulfate.

Clinical Considerations

Monitor infants exposed to morphine sulfate through breast milk for excess sedation and respiratory depression. Withdrawal symptoms can occur in breastfed infants when maternal administration of an opioid analgesic is stopped, or when breast-feeding is stopped.

8.3 Females and Males of Reproductive Potential

Infertility

Chronic use of opioids may cause reduced fertility in females and males of reproductive potential. It is not known whether these effects on fertility are reversible [see Adverse Reactions (6.2), Clinical Pharmacology (12.2)].

In published animal studies, morphine administration adversely effected fertility and reproductive endpoints in male rats and prolonged estrus cycle in female rats [see Nonclinical Toxicology (13)].

8.4 Pediatric Use

The safety and effectiveness in pediatric patients below the age of 18 have not been established.

8.5 Geriatric Use

The pharmacokinetics of morphine sulfate have not been studied in elderly patients. Clinical studies of morphine sulfate did not include sufficient numbers of subjects aged 65 and over to determine whether they respond differently from younger subjects.

Elderly patients (aged 65 years or older) may have increased sensitivity to morphine. In general, use caution when selecting a dosage for an elderly patient, usually starting at the low end of the dosing range, reflecting the greater frequency of decreased hepatic, renal, or cardiac function and of concomitant disease or other drug therapy.

Respiratory depression is the chief risk for elderly patients treated with opioids, and has occurred after large initial doses were administered to patients who were not opioid-tolerant or when opioids were co-administered with other agents that depress respiration. Titrate the dosage of morphine sulfate slowly in geriatric patients and monitor closely for signs of central nervous system and respiratory depression [see Warnings and Precautions (5.6)].

Morphine is known to be substantially excreted by the kidney, and the risk of adverse reactions to this drug may be greater in patients with impaired renal function. Because elderly patients are more likely to have decreased renal function, care should be taken in dose selection, and it may be useful to monitor renal function.

8.6 Hepatic Impairment

Morphine pharmacokinetics have been reported to be significantly altered in patients with cirrhosis. Start these patients with a lower than usual dosage of morphine sulfate and titrate slowly while monitoring for signs of respiratory depression, sedation, and hypotension [see Clinical Pharmacology (12.3)].

8.7 Renal Impairment

Morphine pharmacokinetics are altered in patients with renal failure. Start these patients with a lower than usual dosage of morphine sulfate and titrate slowly while monitoring for signs of respiratory depression, sedation, and hypotension [see Clinical Pharmacology (12.3)].

9 DRUG ABUSE AND DEPENDENCE

9.1 Controlled Substance

Morphine sulfate extended-release tablets contain morphine, a Schedule II controlled substance.

9.2 Abuse

Morphine sulfate extended-release tablets contains morphine, a substance with a high potential for abuse similar to other opioids including fentanyl, hydrocodone, hydromorphone, methadone, oxycodone, oxymorphone, and tapentadol. Morphine sulfate can be abused and is subject to misuse, addiction, and criminal diversion [see Warnings and Precautions (5.1)].

The high drug content in extended-release formulations adds to the risk of adverse outcomes from abuse and misuse.

All patients treated with opioids require careful and frequent reevaluation for signs of misuse, abuse, and addiction, because use of opioid analgesic products carries the risk of addiction even under appropriate medical use. Patients at high risk of morphine sulfate extended-release tablets abuse include those with a history of prolonged use of any opioid, including products containing morphine sulfate, those with a history of drug or alcohol abuse, or those who use morphine sulfate extended-release tablets in combination with other abused drugs.

Prescription drug abuse is the intentional non-therapeutic use of an over-the-counter or prescription drug, even once, for its rewarding psychological or physiological effects. Drug addiction is a cluster of behavioral, cognitive, and physiological phenomena that develop after repeated substance use and includes: a strong desire to take the drug, difficulties in controlling its use, persisting in its use despite harmful consequences, a higher priority given to drug use than to other activities and obligations, increased tolerance, and sometimes a physical withdrawal.

“Drug-seeking” behavior is very common in persons with substance use disorders. Drug-seeking tactics include emergency calls or visits near the end of office hours, refusal to undergo appropriate examination, testing, or referral, repeated “loss” of prescriptions, tampering with prescriptions and reluctance to provide prior medical records or contact information for other healthcare provider(s). “Doctor shopping” (visiting multiple prescribers to obtain additional prescriptions) is common among drug abusers and people suffering from untreated addiction. Preoccupation with achieving adequate pain relief can be appropriate behavior in a patient with poor pain control.

Abuse and addiction are separate and distinct from physical dependence and tolerance. Healthcare providers should be aware that addiction may not be accompanied by concurrent tolerance and symptoms of physical dependence in all addicts. In addition, abuse of opioids can occur in the absence of true addiction.

Morphine sulfate, like other opioids, can be diverted for nonmedical use into illicit channels of distribution. Careful record-keeping of prescribing information, including quantity, frequency, and renewal requests, as required by state federal law, is strongly advised.

Proper assessment of the patient, proper prescribing practices, periodic reevaluation of therapy, and proper dispensing and storage are appropriate measures that help to limit abuse of opioid drugs.

Risks Specific to Abuse of Morphine Sulfate

Morphine sulfate extended-release tablets are for oral use only. Abuse of morphine sulfate poses a risk of overdose and death. This is increased with concurrent use of morphine sulfate with alcohol and/or other CNS depressants. Taking cut, broken, chewed, crushed, or dissolved morphine sulfate extended-release tablets enhances drug release and increases the risk of overdose and death.

Due to the presence of talc as one of the excipients in morphine sulfate, with parenteral abuse the inactive ingredients can result in local tissue necrosis, infection, pulmonary granulomas, increased risk of endocarditis and valvular heart injury, embolism, and death. Parenteral drug abuse is commonly associated with transmission of infectious diseases such as hepatitis and HIV.

9.3 Dependence

Both tolerance and physical dependence can develop during chronic opioid therapy. Tolerance is the need for increasing doses of opioids to maintain a defined effect such as analgesia (in the absence of disease progression or other external factors). Tolerance may occur to both the desired and undesired effects of drugs, and may develop at different rates for different effects.

Physical dependence is a physiological state in which the body adapts to the drug after a period of regular exposure, resulting in withdrawal symptoms after abrupt discontinuation or a significant dosage reduction of a drug. Withdrawal also may be precipitated through the administration of drugs with opioid antagonist activity, (e.g., naloxone, nalmefene), mixed agonist/antagonist analgesics (e.g., pentazocine, butorphanol, nalbuphine), or partial agonists (e.g., buprenorphine). Physical dependence may not occur to a clinically significant degree until after several days to weeks of continued opioid usage.

Do not abruptly discontinue morphine sulfate in a patient physically dependent on opioids. Rapid tapering of morphine sulfate in a patient physically dependent on opioids may lead to serious withdrawal symptoms, uncontrolled pain, and suicide. Rapid discontinuation has also been associated with attempts to find other sources of opioid analgesics, which may be confused with drug-seeking for abuse.

When discontinuing morphine sulfate, gradually taper the dosage using a patient-specific plan that considers the following: the dose of morphine sulfate the patient has been taking, the duration of treatment, and the physical and psychological attributes of the patient. To improve the likelihood of a successful taper and minimize withdrawal symptoms, it is important that the opioid tapering schedule is agreed upon by the patient. In patients taking opioids for a long duration at high doses, ensure that a multimodal approach to pain management, including mental health support (if needed), is in place prior to initiating an opioid analgesic taper [see Dosage and Administration (2.6), Warnings and Precautions (5.13)].

Infants born to mothers physically dependent on opioids will also be physically dependent and may exhibit respiratory difficulties and withdrawal signs [see Use in Specific Populations (8.1)].

10 OVERDOSAGE

Clinical Presentation

Acute overdosage with morphine can be manifested by respiratory depression, somnolence progressing to stupor or coma, skeletal muscle flaccidity, cold and clammy skin, constricted pupils, and, in some cases, pulmonary edema, bradycardia, hypotension, partial or complete airway obstruction, atypical snoring, and death. Marked mydriasis rather than miosis may be seen with hypoxia in overdose situations.

Treatment of Overdose

In case of overdose, priorities are the reestablishment of a patent and protected airway and institution of assisted or controlled ventilation, if needed. Employ other supportive measures (including oxygen and vasopressors) in the management of circulatory shock and pulmonary edema as indicated. Cardiac arrest or arrhythmias will require advanced life support measures.

Opioid antagonists, such as naloxone, are specific antidotes to respiratory depression resulting from opioid overdose. For clinically significant respiratory or circulatory depression secondary to opioid overdose, administer an opioid antagonist.

Because the duration of reversal would be expected to be less than the duration of action of morphine in morphine sulfate, carefully monitor the patient until spontaneous respiration is reliably reestablished. Morphine sulfate will continue to release morphine and add to the morphine load for 24 to 48 hours or longer following ingestion, necessitating prolonged monitoring. If the response to opioid antagonists is suboptimal or only brief in nature, administer additional antagonist as directed by the product’s prescribing information.

In an individual physically dependent on opioids, administration of the recommended usual dosage of the antagonist will precipitate an acute withdrawal syndrome. The severity of the withdrawal symptoms experienced will depend on the degree of physical dependence and the dose of the antagonist administered. If a decision is made to treat serious respiratory depression in the physically dependent patient, administration of the antagonist should be initiated with care and by titration with smaller than usual doses of the antagonist.

11 DESCRIPTION

Morphine sulfate extended-release tablets are for oral use and contains morphine sulfate, an opioid agonist.
Each tablet contains the following inactive ingredients common to all strengths: colloidal silicon dioxide, hypromellose, lactose monohydrate, magnesium stearate, povidone, stearic acid, talc and titanium dioxide.
The tablet strengths describe the amount of morphine per tablet as the pentahydrated sulfate salt (morphine sulfate, USP).
The 15 mg tablets also contain: FD&C Blue # 2/Indigo carmine aluminum lake, ferrosoferric oxide, macrogol/PEG 4000 and macrogol/PEG 400
The 30 mg tablets also contain: D&C Red # 27/Phloxine aluminum lake, FD&C Blue # 2/Indigo carmine aluminum lake, macrogol/PEG 4000 and macrogol/PEG 400
The 60 mg tablets also contain: FD&C Yellow # 6 aluminum lake and macrogol/PEG 4000 and macrogol/PEG 400
The 100 mg tablets also contain: FD&C Blue # 2/Indigo carmine aluminum lake, ferrosoferric oxide, ferric oxide yellow, macrogol/PEG 4000 and macrogol/PEG 400
The 200 mg tablets also contain: D&C Yellow # 10 aluminum lake, FD&C Blue # 2/Indigo carmine aluminum lake, macrogol/PEG 4000 and macrogol/PEG 400

Morphine sulfate, USP are white, feathery, silky crystals, cubical masses of crystals, or white crystalline powder, soluble in water, freely soluble in hot water, slightly soluble in alcohol but more so in hot alcohol, insoluble in chloroform and in ether. The octanol: water partition coefficient of morphine is 1.42 at physiologic pH and the pKb is 7.9 for the tertiary nitrogen (mostly ionized at pH 7.4). Its molecular weight is 758.83 and its structural formula is:

12 CLINICAL PHARMACOLOGY

12.1 Mechanism of Action

Morphine is a full opioid agonist is relatively selective for the mu-opioid receptor, although it can bind to other opioid receptors at higher doses. The principal therapeutic action of morphine is analgesia. Like all full opioid agonists, there is no ceiling effect for analgesia with morphine. Clinically, dosage is titrated to provide adequate analgesia and may be limited by adverse reactions, including respiratory and CNS depression.

The precise mechanism of the analgesic action is unknown. However, specific CNS opioid receptors for endogenous compounds with opioid-like activity have been identified throughout the brain and spinal cord and are thought to play a role in the analgesic effects of this drug.

12.2 Pharmacodynamics

CNS Depressant/Alcohol Interaction

Additive pharmacodynamic effects may be expected when morphine sulfate is used in conjunction with alcohol, other opioids, or illicit drugs that cause central nervous system depression.

Effects on the Central Nervous System

Morphine produces respiratory depression by direct action on brainstem respiratory centers. The respiratory depression involves a reduction in the responsiveness of the brainstem respiratory centers to both increases in carbon dioxide tension and electrical stimulation.

Morphine causes miosis, even in total darkness. Pinpoint pupils are a sign of narcotic overdose but are not pathognomonic (e.g., pontine lesions of hemorrhagic or ischemic origins may produce similar findings). Marked mydriasis rather than miosis may be seen with hypoxia in overdose situations.

Effects on the Gastrointestinal Tract and Other Smooth Muscle

Morphine causes a reduction in motility associated with an increase in smooth muscle tone in the antrum of the stomach and in the duodenum. Digestion of food in the small intestine is delayed and propulsive contractions are decreased. Propulsive peristaltic waves in the colon are decreased, while tone may be increased to the point of spasm, resulting in constipation. Other opioid-induced effects may include reduction in biliary and pancreatic secretions, spasm of the sphincter of Oddi, and transient elevations in serum amylase.

Effects on the Cardiovascular System

Morphine produces peripheral vasodilation which may result in orthostatic hypotension or syncope. Manifestations of histamine release and/or peripheral vasodilation may include pruritus, flushing, red eyes, and sweating, and/or orthostatic hypotension.

Effects on the Endocrine System

Opioids inhibit the secretion of adrenocorticotropic hormone (ACTH), cortisol, and luteinizing hormone (LH) in humans [see Adverse Reaction (6.2)]. They also stimulate prolactin, growth hormone (GH) secretion, and pancreatic secretion of insulin and glucagon.

Chronic use of opioids may influence the hypothalamic-pituitary-gonadal axis, leading to androgen deficiency that may manifest as low libido, impotence, erectile dysfunction, amenorrhea, or infertility. The causal role of opioids in the clinical syndrome of hypogonadism is unknown because the various medical, physical, lifestyle, and psychological stressors that may influence gonadal hormone levels have not been adequately controlled for in studies conducted to date [see Adverse Reactions (6.2)].

Effects on the Immune System

Opioids have been shown to have a variety of effects on components of the immune system in in vitro and animal models. The clinical significance of these findings is unknown. Overall, the effects of opioids appear to be modestly immunosuppressive.

Concentration-Efficacy Relationships

The minimum effective analgesic concentration will vary widely among patients, especially among patients who have been previously treated with potent agonist opioids. The minimum effective analgesic concentration of morphine for any individual patient may increase over time due to an increase in pain, the development of a new pain syndrome, and/or the development of analgesic tolerance [see Dosage and Administration (2.1, 2.3)]

Concentration–Adverse Reaction Relationships

There is a relationship between increasing morphine plasma concentration and increasing frequency of dose-related opioid adverse reactions such as nausea, vomiting, CNS effects, and respiratory depression. In opioid-tolerant patients, the situation may be altered by the development of tolerance to opioid-related adverse reactions [see Dosage and Administration (2.1, 2.3, 2.4)].

12.3 Pharmacokinetics

Absorption

Morphine sulfate is an extended-release tablet containing morphine sulfate. Morphine is released from morphine sulfate extended-release tablets somewhat more slowly than from immediate-release oral preparations. Following oral administration of a given dose of morphine, the amount ultimately absorbed is essentially the same whether the source is morphine sulfate extended-release tablets or an immediate-release formulation. Because of pre-systemic elimination (i.e., metabolism in the gut wall and liver) only about 40% of the administered dose reaches the central compartment.

The oral bioavailability of morphine is approximately 20 to 40%. When morphine sulfateis given on a fixed dosing regimen, steady-state is achieved in about a day.

Food Effect

The effect of food upon the systemic bioavailability of morphine sulfate has not been systematically evaluated for all strengths. One study, conducted with the 30 mg morphine sulfateextended-releasetablets, showed no significant differences in Cmax and AUC (0-24h) values, whether the tablet was taken while fasting or with a high-fat breakfast.

Distribution

Once absorbed, morphine is distributed to skeletal muscle, kidneys, liver, intestinal tract, lungs, spleen, and brain. Morphine also crosses placental membranes and has been found in breast milk. The volume of distribution (Vd) for morphine is approximately 3 to 4 liters per kilogram and morphine is 30 to 35% reversibly bound to plasma proteins.

Elimination

Metabolism

The major pathways of morphine metabolism include glucuronidation to produce metabolites including morphine-3-glucuronide, M3G (about 50%) and morphine-6-glucuronide, M6G (about 5 to 15%) and sulfation in the liver to produce morphine-3-etheral sulfate. A small fraction (less than 5%) of morphine is demethylated. M6G has been shown to have analgesic activity but crosses the blood-brain barrier poorly, while M3G has no significant analgesic activity.

Excretion

The elimination of morphine occurs primarily as renal excretion of M3G and its effective half-life after intravenous administration is normally 2 to 4 hours. Approximately 10% of the dose is excreted unchanged in urine. In some studies involving longer periods of plasma sampling, a longer terminal half-life of about 15 hours was reported. A small amount of the glucuronide conjugate is excreted in the bile, and there is some minor enterohepatic recycling.

Specific Populations

Sex

A sex analysis of pharmacokinetic data from healthy subjects taking morphine sulfate indicated that morphine concentrations were similar in males and females.

Race/Ethnicity

Chinese subjects given intravenous morphine had a higher clearance when compared to Caucasian subjects (1852 +/- 116 ml/min compared to 1495 +/- 80 ml/min).

Hepatic Impairment

Morphine pharmacokinetics are altered in patients with cirrhosis. Clearance was found to decrease with a corresponding increase in half-life. The M3G and M6G to morphine plasma AUC ratios also decreased in these patients, indicating diminished metabolic activity. Adequate studies of the pharmacokinetics of morphine in patients with severe hepatic impairment have not been conducted.

Renal Impairment

Morphine pharmacokinetics are altered in patients with renal failure. The AUC is increased, and clearance is decreased and the metabolites, M3G and M6G, may accumulate to much higher plasma levels in patients with renal failure as compared to patients with normal renal function. Adequate studies of the pharmacokinetics of morphine in patients with severe renal impairment have not been conducted.

13 NONCLINICAL TOXICOLOGY

13.1 Carcinogenesis, Mutagenesis, Impairment of Fertility

Carcinogenesis

Long-term studies in animals to evaluate the carcinogenic potential of morphine have not been conducted.

Mutagenesis

No formal studies to assess the mutagenic potential of morphine have been conducted. In the published literature, morphine was found to be mutagenic in vitro increasing DNA fragmentation in human T-cells. Morphine was reported to be mutagenic in the in vivo mouse micronucleus assay and positive for the induction of chromosomal aberrations in mouse spermatids and murine lymphocytes. Mechanistic studies suggest that the in vivo clastogenic effects reported with morphine in mice may be related to increases in glucocorticoid levels produced by morphine in this species. In contrast to the above positive findings, in vitro studies in the literature have also shown that morphine did not induce chromosomal aberrations in human leukocytes or translocations or lethal mutations in Drosophila.

Impairment of Fertility

No formal nonclinical studies to assess the potential of morphine to impair fertility have been conducted. Several nonclinical studies from the literature have demonstrated adverse effects on male fertility in the rat from exposure to morphine. One study in which male rats were administered morphine sulfate subcutaneously prior to mating (up to 30 mg/kg twice daily) and during mating (20 mg/kg twice daily) with untreated females, a number of adverse reproductive effects including reduction in total pregnancies and higher incidence of pseudopregnancies at 20 mg/kg/day (3.2 times the HDD) were reported.

Studies from the literature have also reported changes in hormonal levels in male rats (i.e. testosterone, luteinizing hormone) following treatment with morphine at 10 mg/kg/day or greater (1.6 times the HDD).

Female rats that were administered morphine sulfate intraperitoneally prior to mating exhibited prolonged estrous cycles at 10 mg/kg/day (1.6 times the HDD).

Exposure of adolescent male rats to morphine has been associated with delayed sexual maturation and following mating to untreated females, smaller litters, increased pup mortality, and/or changes in reproductive endocrine status in adult male offspring have been reported (estimated 5 times the plasma levels at the HDD).

16 HOW SUPPLIED/STORAGE AND HANDLING

Morphine sulfate extended-release tablets 100 mg are round, gray-colored, film-coated tablets debossed with “RD” and “73” on one side and plain on the other side. They are supplied as follows:

- NDC 71335-3080-1: 90 TABLETs in a BOTTLE
- NDC 71335-3080-2: 60 TABLETs in a BOTTLE
- NDC 71335-3080-3: 30 TABLETs in a BOTTLE
- NDC 71335-3080-4: 120 TABLETs in a BOTTLE

Store at 20° - 25° C (68° - 77° F) [See USP Controlled Room Temperature].
Store morphine sulfate extended-release tablets securely and dispose of properly [see Patient Counseling Information (17)].
Dispense in a tight, light-resistant container.

Repackaged/Relabeled by:
Bryant Ranch Prepack
Burbank, CA 91504

17 PATIENT COUNSELING INFORMATION

Advise the patient to read the FDA-approved patient labeling (Medication Guide).

Storage and Disposal

Because of the risks associated with accidental ingestion, misuse, and abuse, advise patients to store morphine sulfate extended-release tablets securely, out of sight and reach of children, and in a location not accessible by others, including visitors to the home [see Warnings and Precautions (5.1), Drug Abuse and Dependence (9.2)]. Inform patients that leaving morphine sulfate extended-release tablets unsecured can pose a deadly risk to others in the home.

Advise patients and caregivers that when medicines are no longer needed, they should be disposed of promptly. Expired, unwanted, or unused morphine sulfate extended-release tablets should be disposed of by flushing the unused medication down the toilet if a drug take-back option is not readily available. Inform patients that they can visit www.fda.gov/drugdisposal for a complete list of medicines recommended for disposal by flushing, as well as additional information on disposal of unused medicines.

Addiction, Abuse, and Misuse

Inform patients that the use of morphine sulfate extended-release tablets even when taken as recommended, can result in addiction, abuse, and misuse, which can lead to overdose and death [see Warnings and Precautions (5.1)]. Instruct patients not to share morphine sulfate extended-release tablets with others and to take steps to protect morphine sulfate extended-release tablets from theft or misuse.

Life-Threatening Respiratory Depression

Inform patients of the risk of life-threatening respiratory depression, including information that the risk is greatest when starting morphine sulfate extended-release tablets or when the dosage is increased, and that it can occur even at recommended dosages. Educate patients and caregivers on how to recognize respiratory depression and emphasize the importance of calling 911 or getting emergency medical help right away in the event of a known or suspected overdose [see Warnings and Precautions (5.3)].

Patient Access to Naloxone for the Emergency Treatment of Opioid Overdose

Discuss with the patient and caregiver the availability of naloxone for the emergency treatment of opioid overdose, both when initiating and renewing treatment with morphine sulfate extended-release tablets. Inform patients and caregivers about the various ways to obtain naloxone as permitted by individual state naloxone dispensing and prescribing requirements or guidelines (e.g., by prescription, directly from a pharmacist, or as part of a community-based program) [see Dosage and Administration (2.2), Warnings and Precautions (5.3)].

Educate patients and caregivers on how to recognize the signs and symptoms of an overdose.

Explain to patients and caregivers that naloxone’s effects are temporary, and that they must call 911 or get emergency medical help right away in all cases of known or suspected opioid overdose, even if naloxone is administered [see Overdosage (10)].

If naloxone is prescribed, also advise patients and caregivers:

- How to treat with naloxone in the event of an opioid overdose
- · To tell family and friends about their naloxone and to keep it in a place where family and friends can access it in an emergency
- To read the Patient Information (or other educational material) that will come with their naloxone. Emphasize the importance of doing this before an opioid emergency happens, so the patient and caregiver will know what to do.

Accidental Ingestion

Inform patients that accidental ingestion, especially by children, may result in respiratory depression or death [see Warnings and Precautions (5.3)].

Interactions with Benzodiazepines and Other CNS Depressants

Inform patients and caregivers that potentially fatal additive effects may occur if morphine sulfate extended-release tablets are used with benzodiazepines or other CNS depressants, including alcohol, and not to use these concomitantly unless supervised by a healthcare provider [see Warnings and Precautions (5.5), Drug Interactions (7)].

Serotonin Syndrome

Inform patients that opioids could cause a rare but potentially life-threatening condition resulting from concomitant administration of serotonergic drugs. Warn patients of the symptoms of serotonin syndrome and to seek medical attention right away if symptoms develop. Instruct patients to inform their physicians if they are taking, or plan to take serotonergic medications [see Drug Interactions 7].

MAOI Interaction

Inform patients not to take morphine sulfate extended-release tablets while using any drugs that inhibit monoamine oxidase. Patients should not start MAOIs while taking morphine sulfate extended-release tablets [see Warnings and Precautions (5.7), Drug Interactions (7)].

Adrenal Insufficiency

Inform patients that opioids could cause adrenal insufficiency, a potentially life-threatening condition. Adrenal insufficiency may present with non-specific symptoms and signs such as nausea, vomiting, anorexia, fatigue, weakness, dizziness, and low blood pressure. Advise patients to seek medical attention if they experience a constellation of these symptoms [see Warnings and Precautions (5.8)].

Important Administration Instructions

Instruct patients how to properly take morphine sulfate extended-release tablets, including the following:

- Swallow morphine sulfate extended-release tablets whole [see Dosage and Administration (2.1)]
- Do not crush, chew, or dissolve the tablets [see Dosage and Administration (2.1)]
- Use morphine sulfate extended-release tablets exactly as prescribed to reduce the risk of life-threatening adverse reactions (e.g., respiratory depression) [see Warnings and Precautions (5.3)]

Important Discontinuation Instructions

In order to avoid developing withdrawal symptoms, instruct patients not to discontinue morphine sulfate extended-release tablets without first discussing a tapering plan with the prescriber [see Dosage and Administration (2.6)].

Hypotension

Inform patients that morphine sulfate extended-release tablets may cause orthostatic hypotension and syncope. Instruct patients how to recognize symptoms of low blood pressure and how to reduce the risk of serious consequences should hypotension occur (e.g., sit or lie down, carefully rise from a sitting or lying position) [see Warnings and Precautions (5.9)].

Anaphylaxis

Inform patients that anaphylaxis has been reported with ingredients contained in morphine sulfate extended-release tablets. Advise patients how to recognize such a reaction and when to seek medical attention [see Contraindications (4), Adverse Reactions (6)].

Pregnancy

Neonatal Opioid Withdrawal Syndrome

Inform female patients of reproductive potential that use of morphine sulfate extended-release tablets for an extended period of time during pregnancy can result in neonatal opioid withdrawal syndrome, which may be life-threatening if not recognized and treated [see Warnings and Precautions (5.4), Use in Specific Populations (8.1)].

Embryo-Fetal Toxicity

Inform female patients of reproductive potential that morphine sulfate extended-release tablets can cause fetal harm and to inform their healthcare provider of a known or suspected pregnancy [see Adverse Reactions (6.2)].

Lactation

Advise patients that breastfeeding is not recommended during treatment with morphine sulfate extended-release tablets [see Use in Specific Populations (8.2)]

Infertility

Inform patients that use of opioids for an extended period of time may cause reduced fertility. It is not known whether these effects on fertility are reversible [Use in Specific Populations (8.3)].

Driving or Operating Heavy Machinery

Inform patients that morphine sulfate extended-release tablets may impair the ability to perform potentially hazardous activities such as driving a car or operating heavy machinery. Advise patients not to perform such tasks until they know how they will react to the medication.

Constipation

Advise patients of the potential for severe constipation, including management instructions and when to seek medical attention.

Healthcare professionals can telephone Sun Pharmaceutical Industries Inc. (1-800-818-4555) for information on this product.

Manufactured by:

Ohm Laboratories Inc.

New Brunswick, NJ 08901

Distributed by:

Sun Pharmaceutical Industries, Inc.

Cranbury, NJ 08512

September 2023 FDA-11

MEDICATION GUIDE

MEDICATION GUID

MORPHINE (MOR feen) SULFATE EXTENDED-RELEASE TABLETS, CII

Rx only

Morphine sulfate extended-release tablets are:

- A strong prescription pain medicine that contains an opioid (narcotic) that is used to manage severe and persistent pain that requires an extended treatment period with a daily opioid pain medicine when other do not treat your pain well enough or you cannot tolerate them.
- A long-acting (extended-release) opioid pain medicine that can put you at risk for overdose and death. Even if you take your dose correctly as prescribed you are at risk for opioid addiction, abuse, and misuse that can lead to death.
- Not for use to treat pain that is not around-the-clock.

Important information about morphine sulfate extended-release tablets:

- Get emergency help or call 911 right away if you take too much morphine sulfate extended-release tablets (overdose). When you first start taking morphine sulfate extended-release tablets, when your dose is changed, or if you take too much (overdose), serious or life-threatening breathing problems that can lead to death may occur. Talk to your healthcare provider about naloxone, a medicine for the emergency treatment of an opioid overdose.
- Taking morphine sulfate extended-release tablets with other opioid medicines, benzodiazepines, alcohol, or other central nervous system depressants (including street drugs) can cause severe drowsiness, decreased awareness, breathing problems, coma, and death.
- Never give anyone else your morphine sulfate extended-release tablets. They could die from taking it. Selling or giving away morphine sulfate extended-release tablets is against the law.
- Store morphine sulfate extended-release tablets securely, out of sight and reach of children, and in a location not accessible by others, including visitors to the home.

Do not take morphine sulfate extended-release tablets if you have:

- severe asthma, trouble breathing, or other lung problems.
- a bowel blockage or have narrowing of the stomach or intestines.

Before taking morphine sulfate extended-release tablets, tell your healthcare provider if you have a history of:

• head injury, seizures

• liver, kidney, thyroid problems

• problems urinating

• pancreas or gallbladder problems

• abuse of street or prescription drugs, alcohol addiction,

opioid overdose, or mental health problems.

Tell your healthcare provider if you are:

- noticing your pain getting worse. If your pain gets worse after you take morphine sulfate extended-release tablets, do not take more of morphine sulfate extended-release tablets without first talking to your healthcare provider. Talk to your healthcare provider if the pain that you have increases, if you feel more sensitive to pain, or if you have new pain after taking morphine sulfate extended-release tablets.
- pregnant or planning to become pregnant. Prolonged use of morphine sulfate extended-release tablets during pregnancy can cause withdrawal symptoms in your newborn baby that could be life-threatening if not recognized and treated.
- breastfeeding. Not recommended during treatment with morphine sulfate. It may harm your baby living in a household where there are small children or someone who has abused street or prescription drugs
- taking prescription or over-the-counter medicines, vitamins, or herbal supplements. Taking morphine sulfate extended-release tablets with certain other medicines can cause serious side effects.

When taking morphine sulfate extended-release tablets:

- Do not change your dose. Take morphine sulfate extended-release tablets exactly as prescribed by your healthcare provider. Use the lowest dose possible for the shortest duration.
- Take your prescribed dose every 8 to 12 hours, as directed by your healthcare provider. Do not take more than your prescribed dose. If you miss a dose, take your next dose at the usual time.
- Swallow morphine sulfate extended-release tablets whole. Do not cut, break, chew, crush, dissolve, snort, or inject morphine sulfate extended-release tablets because this may cause you to overdose and die.
- Call your healthcare provider if the dose you are taking does not control your pain.
- Do not stop taking morphine sulfate extended-release tablets without talking to your healthcare provider.

Dispose of expired, unwanted, or unused morphine sulfate extended-release tablets by taking your drug to an authorized DEA-registered collector or drug take-back program. If one is not available, you can dispose of morphine sulfate extended-release tablets by mixing the product with dirt, cat litter, or coffee grounds; placing the mixture in a sealed plastic bag, and throwing the bag in your trash. Visit www.fda.gov/drugdisposal for additional information on disposal of unused medicines.

While taking morphine sulfate extended-release tablets DO NOT:

- Drive or operate heavy machinery,until you know how morphine sulfate extended-release tablets affect you. Morphine sulfate extended-release tablets can make you sleepy, dizzy, or lightheaded.
- Drink alcohol or use prescription or over-the-counter medicines that contain alcohol. Using products containing alcohol during treatment with morphine sulfate extended-release tablets may cause you to overdose and die.

The possible side effects of morphine sulfate extended-release tablets are:

- Constipation, nausea, sleepiness, vomiting, tiredness, headache, dizziness, abdominal pain. Call your healthcare provider if you have any of these symptoms and they are severe.

Get emergency medical help or call 911 right away if you have:

- trouble breathing, shortness of breath, fast heartbeat, chest pain, swelling of your face, tongue or throat, extreme drowsiness, light-headedness when changing positions, feeling faint, agitation, high body temperature, trouble walking, stiff muscles, or mental changes such as confusion.

These are not all the possible side effects of morphine sulfate extended-release tablets. Call your healthcare provider for medical advice about side effects. You may report side effects to FDA at 1-800-FDA-1088. For more information go to dailymed.nlm.nih.gov

This Medication Guide has been approved by the U.S. Food and Drug Administration.

Manufactured by:

Ohm Laboratories Inc.

New Brunswick, NJ 08901

Distributed by:

Sun Pharmaceutical Industries, Inc.

Cranbury, NJ 08512

www.sunpharma.com or call 1-800-818-4555

September 2023

FDA-10

PACKAGE LABEL

Morphine Sulfate Extended-Release 100mg (CII) Tablets